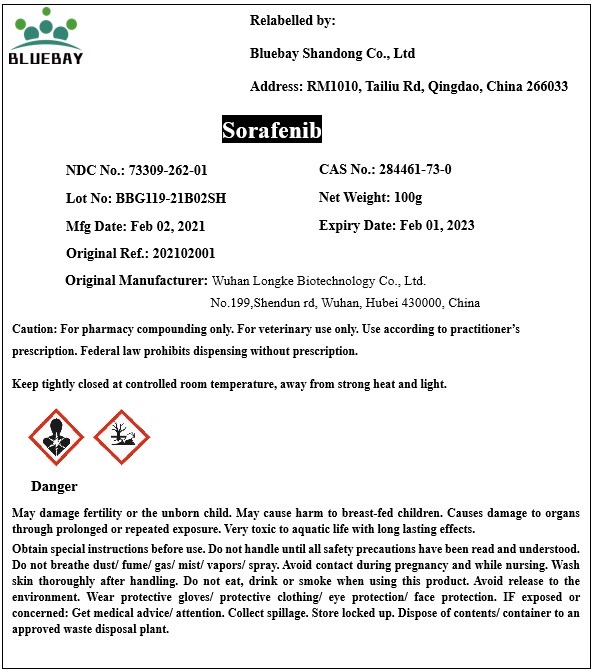 DRUG LABEL: Sorafenib
NDC: 73309-262 | Form: POWDER
Manufacturer: BLUEBAY SHANDONG CO.,LTD
Category: other | Type: BULK INGREDIENT
Date: 20210309

ACTIVE INGREDIENTS: SORAFENIB 1 g/1 g

Sorafenib